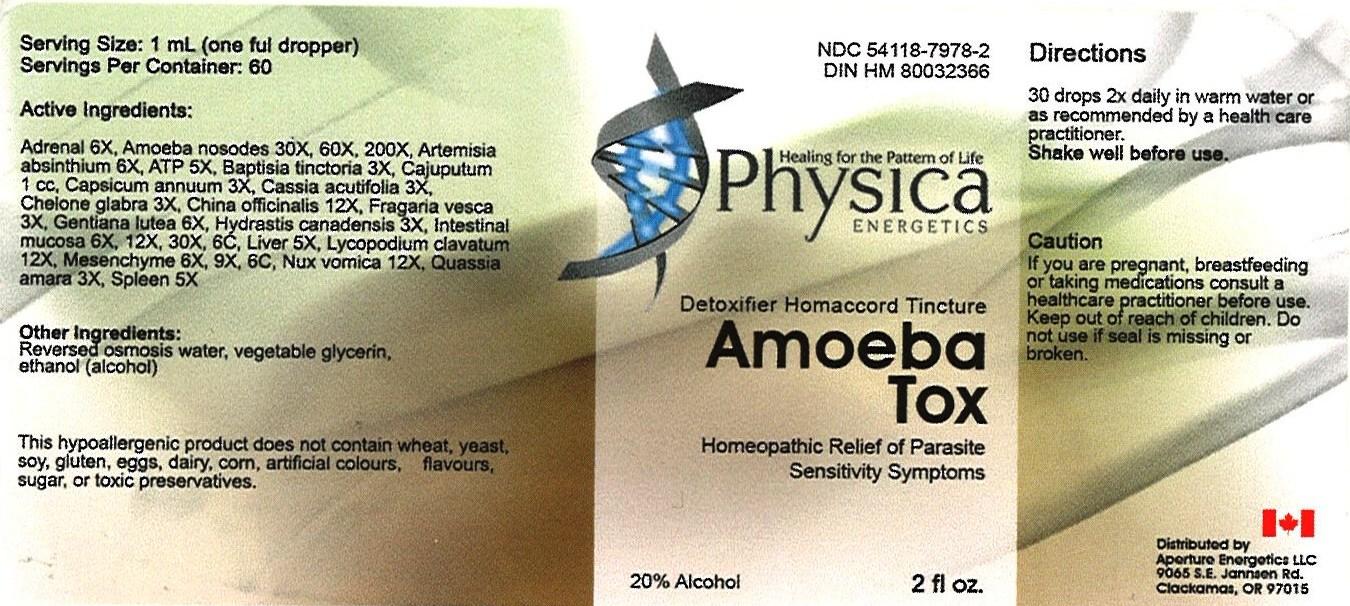 DRUG LABEL: Amoeba Tox
NDC: 54118-7978 | Form: SOLUTION/ DROPS
Manufacturer: ABCO Laboratories, Inc
Category: homeopathic | Type: HUMAN OTC DRUG LABEL
Date: 20121028

ACTIVE INGREDIENTS: BOS TAURUS ADRENAL GLAND 6 [hp_X]/60 mL; ENTAMOEBA HISTOLYTICA 30 [hp_X]/60 mL; WORMWOOD 6 [hp_X]/60 mL; ADENOSINE TRIPHOSPHATE 5 [hp_X]/60 mL; BAPTISIA TINCTORIA 3 [hp_X]/60 mL; CAJUPUT OIL 1 [hp_C]/60 mL; CAPSICUM 3 [hp_X]/60 mL; SENNA LEAF 3 [hp_X]/60 mL; CHELONE GLABRA 3 [hp_X]/60 mL; CINCHONA OFFICINALIS BARK 12 [hp_X]/60 mL; ALPINE STRAWBERRY 3 [hp_X]/60 mL; GENTIANA LUTEA ROOT 6 [hp_X]/60 mL; GOLDENSEAL 3 [hp_X]/60 mL; CEANOTHUS AMERICANUS LEAF 6 [hp_X]/60 mL; MAMMAL LIVER 5 [hp_X]/60 mL; LYCOPODIUM CLAVATUM SPORE 12 [hp_X]/60 mL; BOS TAURUS MESENCHYME 6 [hp_X]/60 mL; STRYCHNOS NUX-VOMICA SEED 12 [hp_X]/60 mL; QUASSIA AMARA WOOD 3 [hp_Q]/60 mL; BOS TAURUS SPLEEN 5 [hp_X]/60 mL
INACTIVE INGREDIENTS: WATER; GLYCERIN; ALCOHOL

Amoeba Tox Homeopathic Liquid

Active Ingredients:

Adrenal 6X

Amoeba nosodes 30X, 60X, 200X

Artemisia absinthium 6X

ATP 5X

Baptisia tinctoria 3X

Cajuputum 1cc

Capsicum annuum 3X

Cassia acutifolia 3X

Chelone glabra 3X

China officinalis 12X

Fragaria vesca 3X

Gentiana lutea 6X

Hydrastis Canadensis 3X

Intentinal mucosa 6X, 12X, 30X, 6C

Liver 5X

Lycopodium clavatum 12X

Mesenchyme 6X, 9X, 6C

Nux vomica 12X

Quassia amara 3X

Spleen 5X

PURPOSE

- Homeopathic Relief of Parasite Sensitivity Symptoms

- Keep out of reach of children

INDICATIONS AND USAGE

- 30 drops 2X daily in warm water
- or as recommended by a health care practitioner
- Shake well before use

WARNINGS

- If you are pregnant, breastfeeding or taking medications consult a healthcare practitioner before use.
- Keep out of reach of children.
- Do not use if seal is missing or broken.

DOSAGE AND ADMINISTRATION

- 30 drops 2X daily
- or as recommended by a health care practitioner
- Shake well before use.

INACTIVE INGREDIENT

- Reversed osmosis water
- vegetable glycerin
- alcohol (ethanol)

PACKAGE LABEL

- amoeba tox.jpg
- image of bottle label